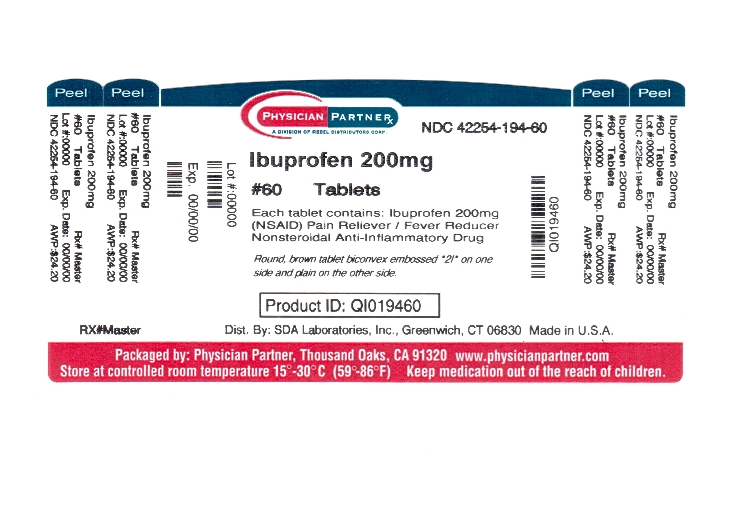 DRUG LABEL: Ibuprofen
NDC: 42254-194 | Form: TABLET
Manufacturer: Rebel Distributors Corp
Category: otc | Type: HUMAN OTC DRUG LABEL
Date: 20120327

ACTIVE INGREDIENTS: IBUPROFEN 200 mg/1 1
INACTIVE INGREDIENTS: CARNAUBA WAX; SILICON DIOXIDE; CROSCARMELLOSE SODIUM; D&C YELLOW NO. 10; FD&C BLUE NO. 2; FD&C RED NO. 40; FD&C YELLOW NO. 6; HYPROMELLOSES; MAGNESIUM STEARATE; CELLULOSE, MICROCRYSTALLINE; POLYDEXTROSE; POLYETHYLENE GLYCOLS; POLYSORBATE 80; FERRIC OXIDE RED; TITANIUM DIOXIDE

Drug Facts

Active Ingredient (In each tablet)

Ibuprofen 200 mg (NSAID)*

*nonsteroidal anti- inflammatory drug

Purpose

Pain reliever/ fever reducer

Uses

temporarily relieves minor aches and pain due to

- minor pain of arthritis
- headache
- toothache
- backache
- the common cold
- menstrual cramps
- muscular aches
- temporarily reduces fever

Warnings

Allergy alert: Ibuprofen may cause a severe allergic reaction, especially in people allergic to aspirin. Symptoms may include

- hives
- facial swelling
- asthma (wheezing)
- shock
- skin reddening
- rash
- blisters

If an allergic reaction occurs, stop use and seek medical help right away.

Stomach bleeding warning: This product contains an NSAID, which may cause severe stomach bleeding. The chance is higher if you

- are age 60 or older
- have had stomach ulcers or bleeding problems
- take a blood thinning (anticoagulant) or steroid drug
- take other drugs containing prescription or non prescription NSAIDs [aspirin, ibuprofen, naproxen, or others]
- have 3 or more alcoholic drinks everyday while using this product
- take more or for a longer time than directed

Do not use

- if you have ever had an allergic reaction to any other pain reliever/ fever reducer
- right before or after heart surgery

Ask a doctor before use if

- stomach bleeding warning applies to you
- you have problems or serious side effects from taking pain relievers or fever reducers
- you have a history of stomach problems, such as heartburn
- you have high blood pressure, heart disease, liver cirrhosis, kidney disease or asthma
- you are taking a diuretic

Ask a doctor or pharmacist before use if you are

- under a doctor's care for any serious condition
- taking aspirin for heart attack or stroke, because ibuprofen may decrease this benefit of aspirin
- taking any other drug

when using this product

- take food or milk if stomach upset occurs
- the risk of heart attack or stroke may increase if you use more than directed or for longer than directed

stop use and ask a doctor if

- you experience any of the following signs of stomach bleeding
- feel faint
- vomit blood
- have bloody or black stools
- have stomach pain that does not get better
- pain gets worse or last for more than 10 days
- fever gets worse or last more than 3 days
- redness or swelling is present in the painful area
- any new symptoms appear

if pregnant or breast feeding

ask a health professional before use. It is especially important not to use ibuprofen during the last 3 months of pregnancy unless definitely directed to do so by a doctor because it may cause problems in the unborn child or complications during delivery.

keep out of reach of children

In case of overdose, get medical help or contact a poison control center right away.

This package is not for households with young children.

Directions

- do not take more than directed
- the smallest effective dose should be used

Adults and children 12 years and older | - take 1 tablet every4 to 6 hours while symptoms persist - if pain or fever does not respond to 1 tablet, 2 tablets may be used - do not exceed 6 tablets in 24 hours, unless directed by a doctor
children under 12 years | - ask a doctor

other information

- store between 20o- 25oC (68o- 77oF)
- avoid high humidity and excessive heat above 40oC (104oF)

Inactive Ingredients:

carnauba wax, colloidal silicon dioxide, croscarmellose sodium, DC yellow# 10, FDC blue# 2, FDC red# 40, FDC yellow# 6, hypromellose, magnesium stearate, microcrystalline cellulose, polydextrose, polyethylene glycol, polysorbate 80, red iron oxide, titanium dioxide

Questions? Adverse drug event call: (800)687-0176

*This product is not manufactured or distributed by Pfizer Consumer Healthcare, owner of the registered trademark ADVIL®.